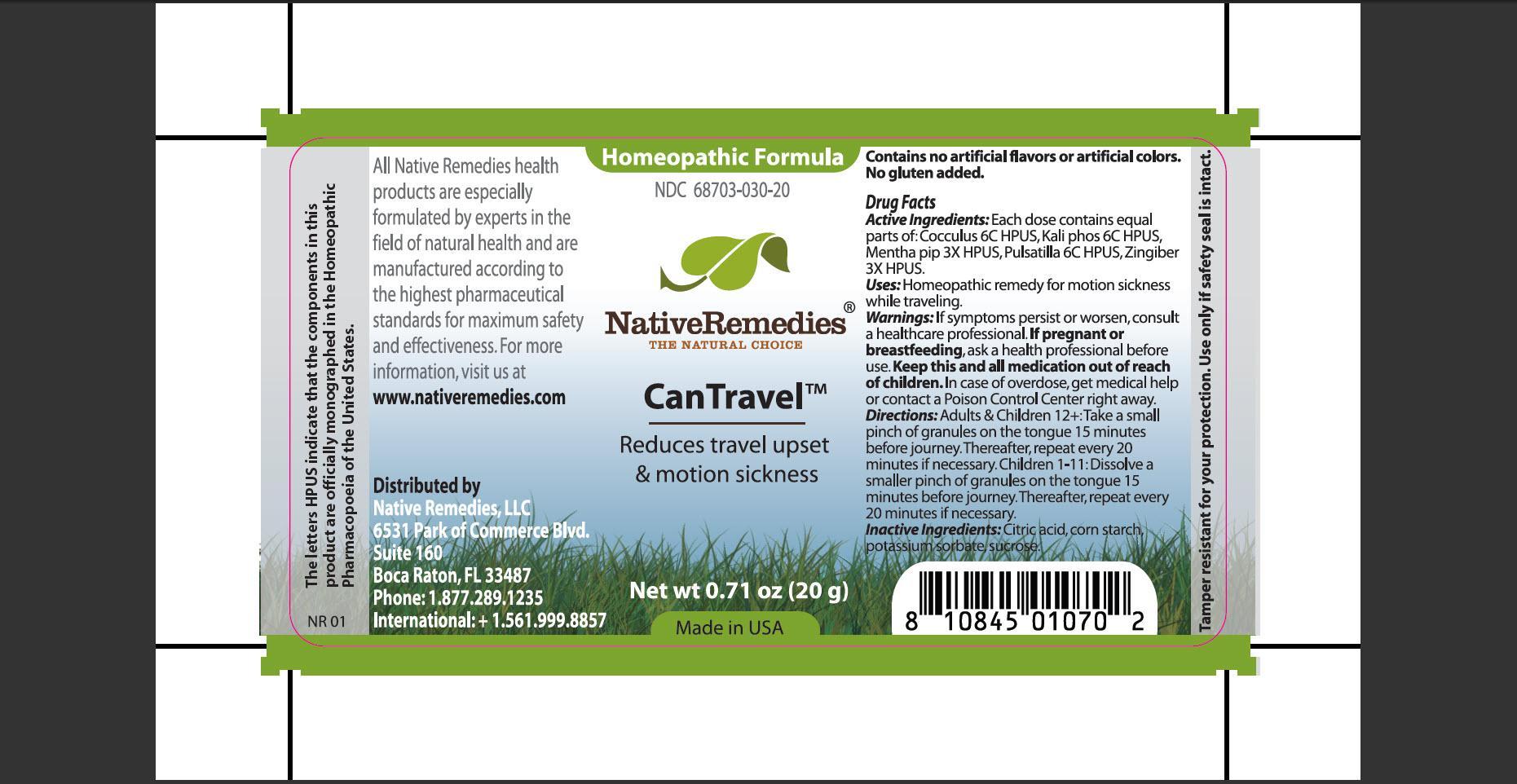 DRUG LABEL: CanTravel
NDC: 68703-030 | Form: GRANULE
Manufacturer: Native Remedies, LLC
Category: homeopathic | Type: HUMAN OTC DRUG LABEL
Date: 20120828

ACTIVE INGREDIENTS: ANAMIRTA COCCULUS SEED 5 [hp_C]/40 mg; POTASSIUM PHOSPHATE, DIBASIC 6 [hp_C]/40 mg; MENTHA PIPERITA 3 [hp_X]/40 mg; PULSATILLA VULGARIS 6 [hp_C]/40 mg; GINGER 3 [hp_X]/40 mg
INACTIVE INGREDIENTS: CITRIC ACID MONOHYDRATE; STARCH, CORN; POTASSIUM SORBATE; SUCROSE

CanTravel

PURPOSE

Reduces travel upset and motion sickness

ACTIVE INGREDIENT

Active Ingredients: Each dose contains equal parts of: Cocculus 6C HPUS, Kali phos 6C HPUS, Mentha pip 3X HPUS, Pulsatilla 6C HPUS, Zingiber 3X HPUS.

INDICATIONS AND USAGE

Uses: Homeopathic remedy for motion sickness while traveling.

WARNINGS

Warnings: If symptoms persist or worsen, consult a healthcare professional.

PREGNANCY OR BREAST FEEDING

If pregnant or breastfeeding, ask a health professional before use.

KEEP OUT OF REACH OF CHILDREN

Keep this and all medication out of reach of children.

OVERDOSAGE

In case of overdose, get medical help or contact a Poison Control Center right away.

DOSAGE AND ADMINISTRATION

Directions: Adults and Children 12+: Take a small pinch of granules on the tongue 15 minutes before journey. Thereafter, repeat every 20 minutes if necessary. Children 1-11: Dissolve a smaller pinch of granules on the tongue 15 minutes before journey. Thereafter, repeat every 20 minutes if necessary.

INACTIVE INGREDIENT

Inactive Ingredients: Citric acid, corn starch, potassium sorbate, sucrose.

PATIENT COUNSELING INFORMATION

The letters HPUS indicate that the components in this product are officially monographed in the Homeopathic Pharmacopoeia of the United States.

All Native Remedies health products are especially formulated by experts in the field of natural health and are manufactured according to the highest pharmaceutical standards for maximum safety and effectiveness. For more information, visit us at www.nativeremedies.com

Distributed by
Native Remedies, LLC
6531 Park of Commerce Blvd.
Suite 160
Boca Raton, FL 33487
Phone: +1.877.289.1235
International: +1.561.999.8857

Contains no artificial flavors or artificial colors. No gluten added.

STORAGE AND HANDLING

Tamper resistant for your protection. Use only if safety seal is intact.